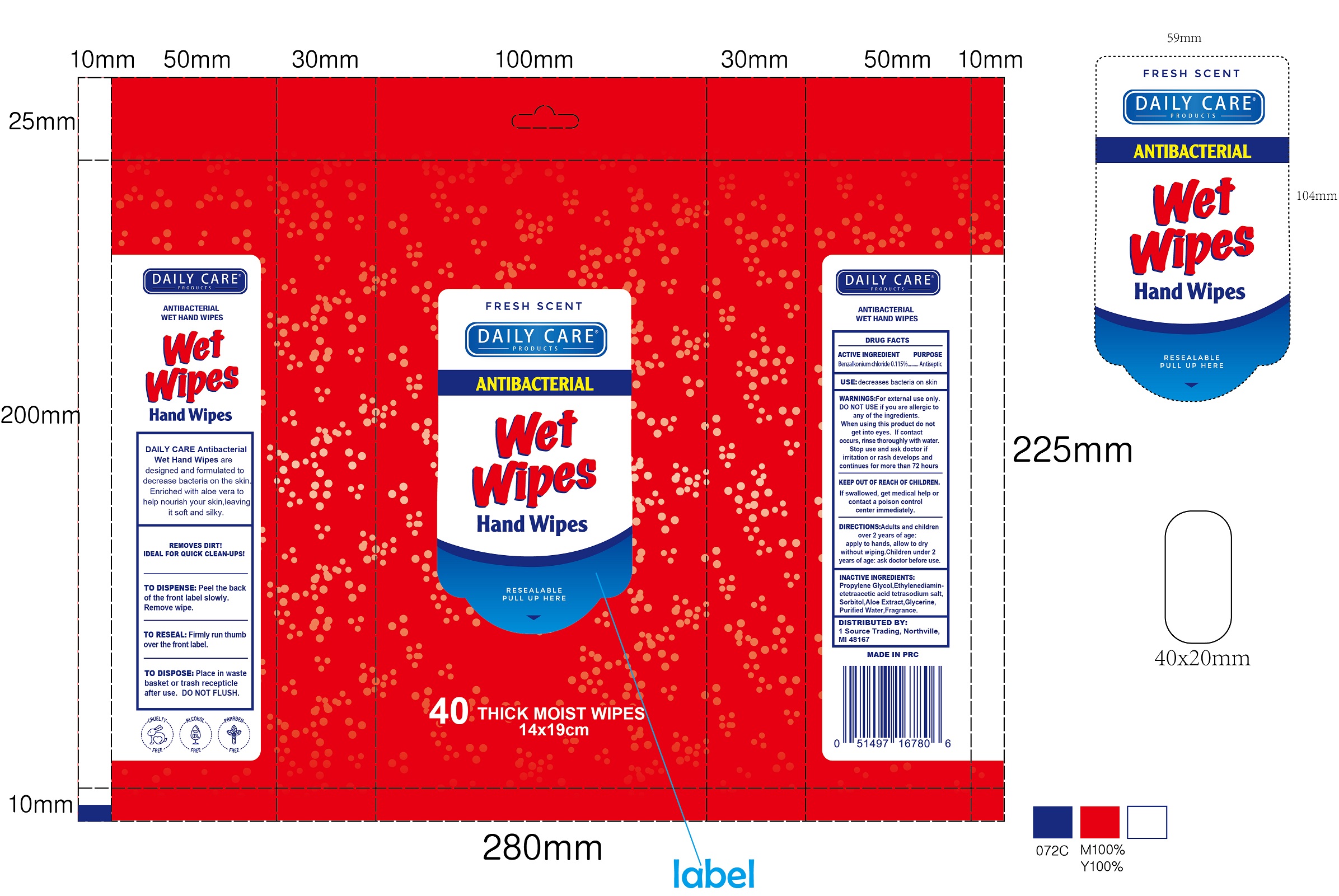 DRUG LABEL: Daily Care Antibacterial Wet Hand
NDC: 78107-000 | Form: CLOTH
Manufacturer: 1 Source Trading LLC
Category: otc | Type: HUMAN OTC DRUG LABEL
Date: 20200627

ACTIVE INGREDIENTS: BENZALKONIUM CHLORIDE 1.15 mg/1 g
INACTIVE INGREDIENTS: PROPYLENE GLYCOL; SORBITOL; ALOE; GLYCERIN; WATER

Daily Care Antibacterial Wet Wipes Hand Wipes

ACTIVE INGREDIENT

Benzalkonium chloride 0.115%

PURPOSE

Antiseptic

USE:

decreases bacteria on skin

WARNINGS:

For external use only.

DO NOT USE

if you are allergic to any of the ingredients.

When using this product

do not get into eyes. If contact occurs, rinse thoroughly with water.

Stop use and ask a doctor if

irritation or rash develops and continues for more than 72 hours

KEEP OUT OF REACH OF CHILDREN.

If swallowed, get medical help or contact a poison control center immediately.

DIRECTIONS:

Adults and children over 2 years of age: apply to hands, allow to dry without wiping. Children under 2 years of age: ask doctor before use.

INACTIVE INGREDIENTS:

Propylene Glycol,Ethylenediaminetetraacetic acid tetrasodium salt, Sorbitol,Aloe Extract,Glycerine, Purified Water,Fragrance.